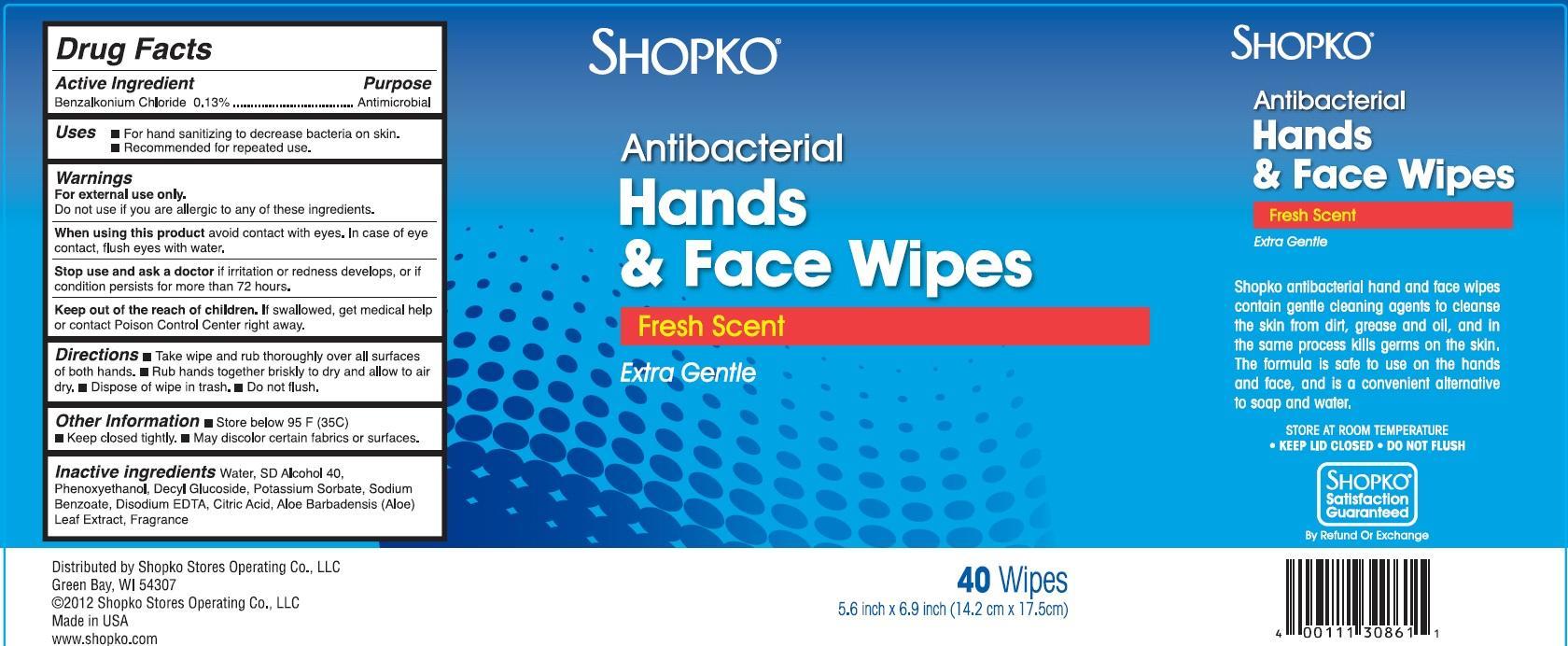 DRUG LABEL: SHOPKO Antibacterial Hands and Face
NDC: 37012-100 | Form: CLOTH
Manufacturer: Shopko Stores Operating Co., LLC.
Category: otc | Type: HUMAN OTC DRUG LABEL
Date: 20121105

ACTIVE INGREDIENTS: BENZALKONIUM CHLORIDE 0.13 g/1 1
INACTIVE INGREDIENTS: WATER; PHENOXYETHANOL; DECYL GLUCOSIDE; POTASSIUM SORBATE; SODIUM BENZOATE; EDETATE DISODIUM; CITRIC ACID MONOHYDRATE; ALOE VERA LEAF

Drug Facts

Active Ingredient

Benzalkonium Chloride 0.13%

Purpose

Antimicrobial

Uses

- For hand sanitizing to decrease bacteria on skin.
- Recommended for repeated use.

Warnings

For external use only.

Do not use if you are allergic to any of these ingredients.

When using this product

avoid contact with eyes. In case of eye contact, flush eyes with water.

Stop use and ask a doctor

if irritation or redness develpos, or if condition persists for more than 72 hours.

Keep out of reach of children.

If swallowed , get medical help or contact Poison Control Center right away.

Directions

- Take wipe and rub throughly over all surfaces of both hands.
- Rub hands together briskly to dry and allow to air dry.
- Dispose of wipe in trash.
- Do not flush.

Other Information

- Store below 95 F(35C)
- Keep closed tightly
- May discolor certain fabrics or surfaces.

Inactive ingredients

Water, SD Alcohol 40, Phenoxyethanol, Decyl Glucoside, Potassium Sorbate, Sodium Benzoate, Disodium EDTA, Citric Acid, Aloe Barbadensis (Aloe) Leaf Extract, Fragrance

Principal Display Panel

SHOPKO

Antibacterial

Hands

and Face Wipes

Fresh Scent

Extra Gentle

40 Wipes

5.6 inch X 6.9 inch (14.2 cm X 17.5 cm)